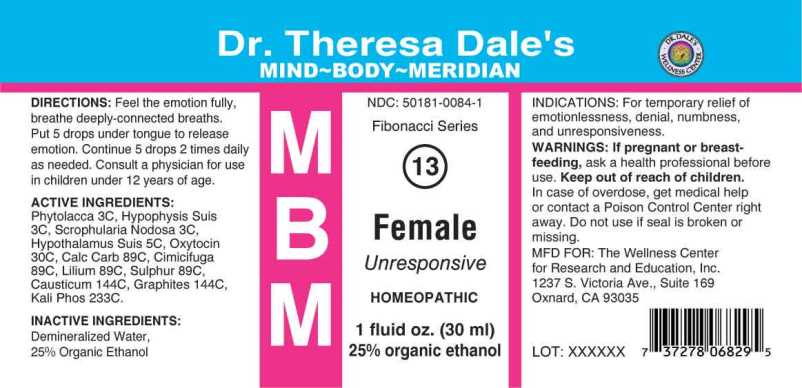 DRUG LABEL: MBM 13 Female
NDC: 50181-0084 | Form: LIQUID
Manufacturer: The Wellness Center for Research and Education, Inc.
Category: homeopathic | Type: HUMAN OTC DRUG LABEL
Date: 20250606

ACTIVE INGREDIENTS: PHYTOLACCA AMERICANA ROOT 3 [hp_C]/1 mL; SUS SCROFA PITUITARY GLAND 3 [hp_C]/1 mL; SCROPHULARIA NODOSA WHOLE 3 [hp_C]/1 mL; BOS TAURUS HYPOTHALAMUS 5 [hp_C]/1 mL; OYSTER SHELL CALCIUM CARBONATE, CRUDE 89 [hp_C]/1 mL; BLACK COHOSH 89 [hp_C]/1 mL; LILIUM LANCIFOLIUM WHOLE FLOWERING 89 [hp_C]/1 mL; SULFUR 89 [hp_C]/1 mL; CAUSTICUM 144 [hp_C]/1 mL; GRAPHITE 144 [hp_C]/1 mL; DIBASIC POTASSIUM PHOSPHATE 233 [hp_C]/1 mL
INACTIVE INGREDIENTS: WATER; ALCOHOL

Drug Facts:

ACTIVE INGREDIENT:

Phytolacca Decandra 3C, Hypophysis (SUIS) 3C, Scrophularia Nodosa 3C, Hypothalamus (SUIS) 5C, Calcarea Carbonica 89C, Cimicifuga Racemosa 89C, Lilium Tigrinum 89C, Sulphur 89C, Causticum 144C, Graphites 144C, Kali Phosphoricum 233C

INDICATIONS:

For the temporary relief of emotionlessness, denial, numbness, and unresponsiveness.

WARNINGS:

If pregnant or breast-feeding, ask a health care professional before use.

Keep out of reach of children. In case of overdose, get medical help or contact a Poison Control Center right away.

Do not use if seal is broken or missing.

Keep out of reach of children. In case of overdose, get medical help or contact a Poison Control Center right away.

DIRECTIONS:

Feel the emotion fully, breathe deeply-connecting breaths. Put 5 drops under tongue to release emotion. Continue 5 drops 2 times daily as needed. Consult a physician for use in children under 12 years of age.

INDICATIONS:

For the temporary relief of emotionlessness, denial, numbness, and unresponsiveness.

INACTIVE INGREDIENTS:

Demineralized Water, 25% Ethanol.

QUESTIONS:

MFD FOR:

The Wellness Center for Research and Education, Inc.

1237 S. Victoria Ave. Suite 169

Oxnard, CA 93035

PACKAGE LABEL DISPLAY

NDC: 50181-0084-1

Fibonacci Series

13

Female

Unresponsive

HOMEOPATHIC

1 fluid oz. (30 ml)